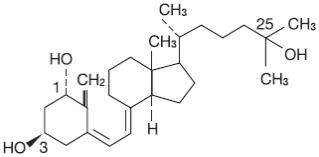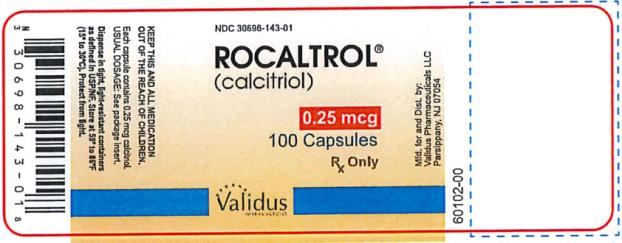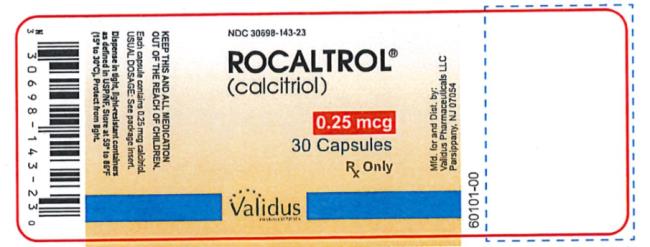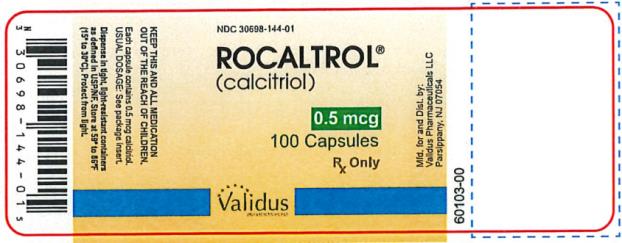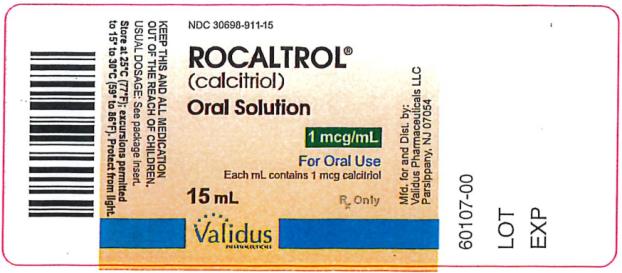 DRUG LABEL: Rocaltrol
NDC: 30698-143 | Form: CAPSULE, GELATIN COATED
Manufacturer: Validus Pharmaceuticals LLC
Category: prescription | Type: HUMAN PRESCRIPTION DRUG LABEL
Date: 20231215

ACTIVE INGREDIENTS: CALCITRIOL 0.25 ug/1 1
INACTIVE INGREDIENTS: BUTYLATED HYDROXYANISOLE; BUTYLATED HYDROXYTOLUENE; COCONUT OIL; GLYCERIN; SORBITOL; FD&C YELLOW NO. 6; TITANIUM DIOXIDE

ROCALTROL

ROCALTROL®
brand of
(Calcitriol)
CAPSULES and ORAL SOLUTION

Rx Only

DESCRIPTION

Rocaltrol (calcitriol) is a synthetic vitamin D analog which is active in the regulation of the absorption of calcium from the gastrointestinal tract and its utilization in the body. Rocaltrol is available as capsules containing 0.25 mcg or 0.5 mcg calcitriol and as an oral solution containing 1 mcg/mL of calcitriol. All dosage forms contain butylated hydroxyanisole (BHA) and butylated hydroxytoluene (BHT) as antioxidants. The capsules contain a fractionated triglyceride of coconut oil, and the oral solution contains a fractionated triglyceride of palm seed oil. Gelatin capsule shells contain glycerin, and sorbitol, with the following dye systems: 0.25 mcg - FD&C Yellow No. 6 and titanium dioxide; 0.5 mcg - FD&C Red No. 3, FD&C Yellow No. 6 and titanium dioxide. The oral solution contains no additional adjuvants or coloring principles.

Calcitriol is a white, crystalline compound which occurs naturally in humans. It has a calculated molecular weight of 416.65 and is soluble in organic solvents but relatively insoluble in water. Chemically, calcitriol is 9,10-seco(5Z,7E)-5,7,10(19)-cholestatriene-1α, 3β, 25-triol and has the following structural formula:

The other names frequently used for calcitriol are 1α,25-dihydroxycholecalciferol, 1,25-dihydroxyvitamin D3, 1,25-DHCC, 1,25(OH)2D3 and 1,25-diOHC.

CLINICAL PHARMACOLOGY

Man's natural supply of vitamin D depends mainly on exposure to the ultraviolet rays of the sun for conversion of 7-dehydrocholesterol in the skin to vitamin D3 (cholecalciferol). Vitamin D3 must be metabolically activated in the liver and the kidney before it is fully active as a regulator of calcium and phosphorus metabolism at target tissues. The initial transformation of vitamin D3 is catalyzed by a vitamin D3-25-hydroxylase enzyme (25-OHase) present in the liver, and the product of this reaction is 25-hydroxyvitamin D3 [25-(OH) D3]. Hydroxylation of 25-(OH) D3 occurs in the mitochondria of kidney tissue, activated by the renal 25-hydroxyvitamin D3-1 alpha-hydroxylase (alpha-OHase), to produce 1,25-(OH)2D3 (calcitriol), the active form of vitamin D3. Endogenous synthesis and catabolism of calcitriol, as well as physiological control mechanisms affecting these processes, play a critical role regulating the serum level of calcitriol. Physiological daily production is normally 0.5 to 1.0 mcg and is somewhat higher during periods of increased bone synthesis (e.g., growth or pregnancy).

Pharmacodynamics

The two known sites of action of calcitriol are intestine and bone. A calcitriol receptor-binding protein appears to exist in the mucosa of human intestine. Additional evidence suggests that calcitriol may also act on the kidney and the parathyroid glands. Calcitriol is the most active known form of vitamin D3 in stimulating intestinal calcium transport. In acutely uremic rats calcitriol has been shown to stimulate intestinal calcium absorption.

The kidneys of uremic patients cannot adequately synthesize calcitriol, the active hormone formed from precursor vitamin D. Resultant hypocalcemia and secondary hyperparathyroidism are a major cause of the metabolic bone disease of renal failure. However, other bone-toxic substances which accumulate in uremia (e.g., aluminum) may also contribute.

The beneficial effect of Rocaltrol in renal osteodystrophy appears to result from correction of hypocalcemia and secondary hyperparathyroidism. It is uncertain whether Rocaltrol produces other independent beneficial effects. Rocaltrol treatment is not associated with an accelerated rate of renal function deterioration. No radiographic evidence of extraskeletal calcification has been found in predialysis patients following treatment. The duration of pharmacologic activity of a single dose of calcitriol is about 3 to 5 days.

Pharmacokinetics

Absorption

Calcitriol is rapidly absorbed from the intestine. Peak serum concentrations (above basal values) were reached within 3 to 6 hours following oral administration of single doses of 0.25 to 1.0 mcg of Rocaltrol. Following a single oral dose of 0.5 mcg, mean serum concentrations of calcitriol rose from a baseline value of 40.0±4.4 (SD) pg/mL to 60.0±4.4 pg/mL at 2 hours, and declined to 53.0±6.9 at 4 hours, 50±7.0 at 8 hours, 44±4.6 at 12 hours, and 41.5±5.1 at 24 hours.

Following multiple-dose administration, serum calcitriol levels reached steady-state within 7 days.

Distribution

Calcitriol is approximately 99.9% bound in blood. Calcitriol and other vitamin D metabolites are transported in blood, by an alpha-globulin vitamin D binding protein. There is evidence that maternal calcitriol may enter the fetal circulation. Calcitriol is transferred into human breast milk at low levels (i.e., 2.2±0.1 pg/mL).

Metabolism

In vivo and in vitro studies indicate the presence of two pathways of metabolism for calcitriol. The first pathway involves the 24-hydroxylase as the first step in catabolism of calcitriol. There is definite evidence of 24-hydroxylase activity in the kidney; this enzyme is also present in many target tissues which possess the vitamin D receptor such as the intestine. The end product of this pathway is a side chain shortened metabolite, calcitroic acid. The second pathway involves the conversion of calcitriol via the stepwise hydroxylation of carbon-26 and carbon-23, and cyclization to yield ultimately 1α, 25R(OH)2-26, 23S-lactone D3. The lactone appears to be the major metabolite circulating in humans, with mean serum concentrations of 131±17 pg/mL. In addition, several other metabolites of calcitriol have been identified: 1α, 25(OH)2-24-oxo-D3; 1α, 23,25(OH)3-24-oxo-D3; 1α, 24R,25(OH)3D3; 1α, 25S,26(OH)3D3; 1α, 25(OH)2-23-oxo-D3; 1α, 25R,26(OH)3-23-oxo-D3; 1α, (OH)24,25,26,27-tetranor-COOH-D3.

Excretion

Enterohepatic recycling and biliary excretion of calcitriol occur. The metabolites of calcitriol are excreted primarily in feces. Following intravenous administration of radiolabeled calcitriol in normal subjects, approximately 27% and 7% of the radioactivity appeared in the feces and urine, respectively, within 24 hours. When a 1-mcg oral dose of radiolabeled calcitriol was administered to normal subjects, approximately 10% of the total radioactivity appeared in urine within 24 hours. Cumulative excretion of radioactivity on the sixth day following intravenous administration of radiolabeled calcitriol averaged 16% in urine and 49% in feces. The elimination half-life of calcitriol in serum after single oral doses is about 5 to 8 hours in normal subjects.

Special Populations

Pediatric Pharmacokinetics

The steady-state pharmacokinetics of oral Rocaltrol were determined in a small group of pediatric patients (age range: 1.8 to 16 years) undergoing peritoneal dialysis. Rocaltrol was administered for 2 months at an average dose of 10.2 ng/kg (SD 5.5 ng/kg). In this pediatric population, mean Cmax was 116 pmol/L, mean serum half-life was 27.4 hours, and mean clearance was 15.3 mL/hr/kg.^1

Geriatric

No studies have examined the pharmacokinetics of calcitriol in geriatric patients.

Gender

Controlled studies examining the influence of gender on calcitriol have not been conducted.

Hepatic Insufficiency

Controlled studies examining the influence of hepatic disease on calcitriol have not been conducted.

Renal Insufficiency

Lower predose and peak calcitriol levels in serum were observed in patients with nephrotic syndrome and in patients undergoing hemodialysis compared with healthy subjects. The elimination half-life of calcitriol increased by at least twofold in chronic renal failure and hemodialysis patients compared with healthy subjects. Peak serum levels in patients with nephrotic syndrome were reached in 4 hours. For patients requiring hemodialysis peak serum levels were reached in 8 to 12 hours; half-lives were estimated to be 16.2 and 21.9 hours, respectively.

INDICATIONS AND USAGE

Predialysis Patients

Rocaltrol is indicated in the management of secondary hyperparathyroidism and resultant metabolic bone disease in patients with moderate to severe chronic renal failure (Ccr 15 to 55 mL/min) not yet on dialysis. In children, the creatinine clearance value must be corrected for a surface area of 1.73 square meters. A serum iPTH level of ≥ 100 pg/mL is strongly suggestive of secondary hyperparathyroidism.

Dialysis Patients

Rocaltrol is indicated in the management of hypocalcemia and the resultant metabolic bone disease in patients undergoing chronic renal dialysis. In these patients, Rocaltrol administration enhances calcium absorption, reduces serum alkaline phosphatase levels, and may reduce elevated parathyroid hormone levels and the histological manifestations of osteitis fibrosa cystica and defective mineralization.

Hypoparathyroidism Patients

Rocaltrol is also indicated in the management of hypocalcemia and its clinical manifestations in patients with postsurgical hypoparathyroidism, idiopathic hypoparathyroidism, and pseudohypoparathyroidism.

CONTRAINDICATIONS

Rocaltrol should not be given to patients with hypercalcemia or evidence of vitamin D toxicity. Use of Rocaltrol in patients with known hypersensitivity to Rocaltrol (or drugs of the same class) or any of the inactive ingredients is contraindicated.

WARNINGS

Overdosage of any form of vitamin D is dangerous (see OVERDOSAGE). Progressive hypercalcemia due to overdosage of vitamin D and its metabolites may be so severe as to require emergency attention. Chronic hypercalcemia can lead to generalized vascular calcification, nephrocalcinosis and other soft-tissue calcification. The serum calcium times phosphate (Ca x P) product should not be allowed to exceed 70 mg^2/dL^2. Radiographic evaluation of suspect anatomical regions may be useful in the early detection of this condition.

Rocaltrol is the most potent metabolite of vitamin D available. The administration of Rocaltrol to patients in excess of their daily requirements can cause hypercalcemia, hypercalciuria, and hyperphosphatemia. Therefore, pharmacologic doses of vitamin D and its derivatives should be withheld during Rocaltrol treatment to avoid possible additive effects and hypercalcemia. If treatment is switched from ergocalciferol (vitamin D2) to calcitriol, it may take several months for the ergocalciferol level in the blood to return to the baseline value (see OVERDOSAGE).

Calcitriol increases inorganic phosphate levels in serum. While this is desirable in patients with hypophosphatemia, caution is called for in patients with renal failure because of the danger of ectopic calcification. A nonaluminum phosphate-binding compound and a low-phosphate diet should be used to control serum phosphorus levels in patients undergoing dialysis.

Magnesium-containing preparations (e.g., antacids) and Rocaltrol should not be used concomitantly in patients on chronic renal dialysis because such use may lead to the development of hypermagnesemia.

Studies in dogs and rats given calcitriol for up to 26 weeks have shown that small increases of calcitriol above endogenous levels can lead to abnormalities of calcium metabolism with the potential for calcification of many tissues in the body.

PRECAUTIONS

General

Excessive dosage of Rocaltrol induces hypercalcemia and in some instances hypercalciuria; therefore, early in treatment during dosage adjustment, serum calcium should be determined twice weekly. In dialysis patients, a fall in serum alkaline phosphatase levels usually antedates the appearance of hypercalcemia and may be an indication of impending hypercalcemia. An abrupt increase in calcium intake as a result of changes in diet (e.g., increased consumption of dairy products) or uncontrolled intake of calcium preparations may trigger hypercalcemia.

Should hypercalcemia develop, treatment with Rocaltrol should be stopped immediately. During periods of hypercalcemia, serum calcium and phosphate levels must be determined daily. When normal levels have been attained, treatment with Rocaltrol can be continued, at a daily dose 0.25 mcg lower than that previously used. An estimate of daily dietary calcium intake should be made and the intake adjusted when indicated. Rocaltrol should be given cautiously to patients on digitalis, because hypercalcemia in such patients may precipitate cardiac arrhythmias.

Immobilized patients, e.g., those who have undergone surgery, are particularly exposed to the risk of hypercalcemia.

In patients with normal renal function, chronic hypercalcemia may be associated with an increase in serum creatinine. While this is usually reversible, it is important in such patients to pay careful attention to those factors which may lead to hypercalcemia. Rocaltrol therapy should always be started at the lowest possible dose and should not be increased without careful monitoring of the serum calcium. An estimate of daily dietary calcium intake should be made and the intake adjusted when indicated.

Patients with normal renal function taking Rocaltrol should avoid dehydration. Adequate fluid intake should be maintained.

Information for Patients

The patient and his or her caregivers should be informed about compliance with dosage instructions, adherence to instructions about diet and calcium supplementation, and avoidance of the use of unapproved nonprescription drugs. Patients and their caregivers should also be carefully informed about the symptoms of hypercalcemia (see ADVERSE REACTIONS).

The effectiveness of Rocaltrol therapy is predicated on the assumption that each patient is receiving an adequate daily intake of calcium. Patients are advised to have a dietary intake of calcium at a minimum of 600 mg daily. The U.S. RDA for calcium in adults is 800 mg to 1200 mg.

Laboratory Tests

For dialysis patients, serum calcium, phosphorus, magnesium, and alkaline phosphatase should be determined periodically. For hypoparathyroid patients, serum calcium, phosphorus, and 24-hour urinary calcium should be determined periodically. For predialysis patients, serum calcium, phosphorus, alkaline phosphatase, creatinine, and intact PTH (iPTH) should be determined initially. Thereafter, serum calcium, phosphorus, alkaline phosphatase, and creatinine should be determined monthly for a 6-month period and then determined periodically. Intact PTH (iPTH) should be determined periodically every 3 to 4 months at the time of visits. During the titration period of treatment with Rocaltrol, serum calcium levels should be checked at least twice weekly (see DOSAGE AND ADMINISTRATION).

Drug Interactions

Cholestyramine

Cholestyramine has been reported to reduce intestinal absorption of fat-soluble vitamins; as such it may impair intestinal absorption of Rocaltrol (see WARNINGS and PRECAUTIONS: General).

Phenytoin/Phenobarbital

The coadministration of phenytoin or phenobarbital will not affect plasma concentrations of calcitriol, but may reduce endogenous plasma levels of 25(OH)D3 by accelerating metabolism. Since blood level of calcitriol will be reduced, higher doses of Rocaltrol may be necessary if these drugs are administered simultaneously.

Thiazides

Thiazides are known to induce hypercalcemia by the reduction of calcium excretion in urine. Some reports have shown that the concomitant administration of thiazides with Rocaltrol causes hypercalcemia. Therefore, precaution should be taken when coadministration is necessary.

Digitalis

Calcitriol dosage must be determined with care in patients undergoing treatment with digitalis, as hypercalcemia in such patients may precipitate cardiac arrhythmias (see PRECAUTIONS: General).

Ketoconazole

Ketoconazole may inhibit both synthetic and catabolic enzymes of calcitriol. Reductions in serum endogenous calcitriol concentrations have been observed following the administration of 300 mg/day to 1200 mg/day ketoconazole for a week to healthy men. However, in vivo drug interaction studies of ketoconazole with Rocaltrol have not been investigated.

Corticosteroids

A relationship of functional antagonism exists between vitamin D analogues, which promote calcium absorption, and corticosteroids, which inhibit calcium absorption.

Phosphate-Binding Agents

Since Rocaltrol also has an effect on phosphate transport in the intestine, kidneys and bones, the dosage of phosphate-binding agents must be adjusted in accordance with the serum phosphate concentration.

Vitamin D

Since calcitriol is the most potent active metabolite of vitamin D3, pharmacological doses of vitamin D and its derivatives should be withheld during treatment with Rocaltrol to avoid possible additive effects and hypercalcemia (see WARNINGS).

Calcium Supplements

Uncontrolled intake of additional calcium-containing preparations should be avoided (see PRECAUTIONS: General).

Magnesium

Magnesium-containing preparations (e.g., antacids) may cause hypermagnesemia and should therefore not be taken during therapy with Rocaltrol by patients on chronic renal dialysis.

Carcinogenesis, Mutagenesis and Impairment of Fertility

Long-term studies in animals have not been conducted to evaluate the carcinogenic potential of Rocaltrol. Rocaltrol is not mutagenic in vitro in the Ames Test, nor is it genotoxic in vivo in the Mouse Micronucleus Test. No significant effects of Rocaltrol on fertility and/or general reproductive performances were observed in a Segment I study in rats at doses of up to 0.3 mcg/kg (approximately 3 times the maximum recommended dose based on body surface area).

Pregnancy

Teratogenic Effects

Rocaltrol has been found to be teratogenic in rabbits when given at doses of 0.08 and 0.3 mcg/kg (approximately 2 and 6 times the maximum recommended dose based on mg/m^2). All 15 fetuses in 3 litters at these doses showed external and skeletal abnormalities. However, none of the other 23 litters (156 fetuses) showed external and skeletal abnormalities compared with controls.

Teratogenicity studies in rats at doses up to 0.45 mcg/kg (approximately 5 times maximum recommended dose based on mg/m^2) showed no evidence of teratogenic potential. There are no adequate and well-controlled studies in pregnant women. Rocaltrol should be used during pregnancy only if the potential benefit justifies the potential risk to the fetus.

Nonteratogenic Effects

In the rabbit, dosages of 0.3 mcg/kg/day (approximately 6 times maximum recommended dose based on surface area) administered on days 7 to 18 of gestation resulted in 19% maternal mortality, a decrease in mean fetal body weight, and a reduced number of newborn surviving to 24 hours. A study of perinatal and postnatal development in rats resulted in hypercalcemia in the offspring of dams given Rocaltrol at doses of 0.08 or 0.3 mcg/kg/day (approximately 1 and 3 times the maximum recommended dose based on mg/m^2), hypercalcemia and hypophosphatemia in dams given Rocaltrol at a dose of 0.08 or 0.3 mcg/kg/day, and increased serum urea nitrogen in dams given Rocaltrol at a dose of 0.3 mcg/kg/day. In another study in rats, maternal weight gain was slightly reduced at a dose of 0.3 mcg/kg/day (approximately 3 times the maximum recommended dose based on mg/m^2) administered on days 7 to 15 of gestation. The offspring of a woman administered 17 mcg/day to 36 mcg/day of Rocaltrol (approximately 17 to 36 times the maximum recommended dose) during pregnancy manifested mild hypercalcemia in the first 2 days of life which returned to normal at day 3.

Nursing Mothers

Calcitriol from ingested Rocaltrol may be excreted in human milk. Because many drugs are excreted in human milk and because of the potential for serious adverse reactions from Rocaltrol in nursing infants, a mother should not nurse while taking Rocaltrol.

Pediatric Use

Safety and effectiveness of Rocaltrol in pediatric patients undergoing dialysis have not been established. The safety and effectiveness of Rocaltrol in pediatric predialysis patients is based on evidence from adequate and well-controlled studies of Rocaltrol in adults with predialysis chronic renal failure and additional supportive data from nonplacebo-controlled studies in pediatric patients. Dosing guidelines have not been established for pediatric patients under 1 year of age with hypoparathyroidism or for pediatric patients less than 6 years of age with pseudohypoparathyroidism (see DOSAGE AND ADMINISTRATION: Hypoparathyroidism).

Oral doses of Rocaltrol ranging from 10 to 55 ng/kg/day have been shown to improve calcium homeostasis and bone disease in pediatric patients with chronic renal failure for whom hemodialysis is not yet required (predialysis). Long-term calcitriol therapy is well tolerated by pediatric patients. The most common safety issues are mild, transient episodes of hypercalcemia, hyperphosphatemia, and increases in the serum calcium times phosphate (Ca x P) product which are managed effectively by dosage adjustment or temporary discontinuation of the vitamin D derivative.

Geriatric Use

Clinical studies of Rocaltrol did not include sufficient numbers of subjects aged 65 and over to determine whether they respond differently from younger subjects. Other reported clinical experience has not identified differences in responses between the elderly and younger patients. In general, dose selection for an elderly patient should be cautious, usually starting at the low end of the dosing range, reflecting the greater frequency of decreased hepatic, renal, or cardiac function, and of concomitant disease or other drug therapy.

ADVERSE REACTIONS

Since Rocaltrol is believed to be the active hormone which exerts vitamin D activity in the body, adverse effects are, in general, similar to those encountered with excessive vitamin D intake, i.e., hypercalcemia syndrome or calcium intoxication, depending on the severity and duration of hypercalcemia (see WARNINGS). Because of the short biological half-life of calcitriol, pharmacokinetic investigations have shown normalization of elevated serum calcium within a few days of treatment withdrawal, i.e., much faster than in treatment with vitamin D3 preparations.

The early and late signs and symptoms of vitamin D intoxication associated with hypercalcemia include:

Early: weakness, headache, somnolence, nausea, vomiting, dry mouth, constipation, muscle pain, bone pain, metallic taste, and anorexia, abdominal pain or stomach ache.

Late: polyuria, polydipsia, anorexia, weight loss, nocturia, conjunctivitis (calcific), pancreatitis, photophobia, rhinorrhea, pruritus, hyperthermia, decreased libido, elevated BUN, albuminuria, hypercholesterolemia, elevated SGOT (AST) and SGPT (ALT), ectopic calcification, nephrocalcinosis, hypertension, cardiac arrhythmias, dystrophy, sensory disturbances, dehydration, apathy, arrested growth, urinary tract infections, and, rarely, overt psychosis.

In clinical studies on hypoparathyroidism and pseudohypoparathyroidism, hypercalcemia was noted on at least one occasion in about 1 in 3 patients and hypercalciuria in about 1 in 7 patients. Elevated serum creatinine levels were observed in about 1 in 6 patients (approximately one half of whom had normal levels at baseline).

In concurrent hypercalcemia and hyperphosphatemia, soft-tissue calcification may occur; this can be seen radiographically (see WARNINGS).

In patients with normal renal function, chronic hypercalcemia may be associated with an increase in serum creatinine (see PRECAUTIONS: General).

Hypersensitivity reactions (pruritus, rash, urticaria, and very rarely severe erythematous skin disorders) may occur in susceptible individuals. One case of erythema multiforme and one case of allergic reaction (swelling of lips and hives all over the body) were confirmed by rechallenge.

To report SUSPECTED ADVERSE REACTIONS, contact Validus Pharmaceuticals LLC at 1-866-982-5438 (1-866-9VALIDUS) or FDA at 1-800-FDA-1088 or www.fda.gov/medwatch.

OVERDOSAGE

Administration of Rocaltrol to patients in excess of their daily requirements can cause hypercalcemia, hypercalciuria, and hyperphosphatemia. Since calcitriol is a derivative of vitamin D, the signs and symptoms of overdose are the same as for an overdose of vitamin D (see ADVERSE REACTIONS). High intake of calcium and phosphate concomitant with Rocaltrol may lead to similar abnormalities. The serum calcium times phosphate (Ca x P) product should not be allowed to exceed 70 mg^2/dL^2. High levels of calcium in the dialysate bath may contribute to the hypercalcemia (see WARNINGS).

Treatment of Hypercalcemia and Overdosage in Dialysis Patients and Hypoparathyroidism Patients

General treatment of hypercalcemia (greater than 1 mg/dL above the upper limit of the normal range) consists of immediate discontinuation of Rocaltrol therapy, institution of a low-calcium diet and withdrawal of calcium supplements. Serum calcium levels should be determined daily until normocalcemia ensues. Hypercalcemia frequently resolves in 2 to 7 days. When serum calcium levels have returned to within normal limits, Rocaltrol therapy may be reinstituted at a dose of 0.25 mcg/day less than prior therapy. Serum calcium levels should be obtained at least twice weekly after all dosage changes and subsequent dosage titration. In dialysis patients, persistent or markedly elevated serum calcium levels may be corrected by dialysis against a calcium-free dialysate.

Treatment of Hypercalcemia and Overdosage in Predialysis Patients

If hypercalcemia ensues (greater than 1 mg/dL above the upper limit of the normal range), adjust dosage to achieve normocalcemia by reducing Rocaltrol therapy from 0.5 mcg to 0.25 mcg daily. If the patient is receiving a therapy of 0.25 mcg daily, discontinue Rocaltrol until patient becomes normocalcemic. Calcium supplements should also be reduced or discontinued. Serum calcium levels should be determined 1 week after withdrawal of calcium supplements. If serum calcium levels have returned to normal, Rocaltrol therapy may be reinstituted at a dosage of 0.25 mcg/day if previous therapy was at a dosage of 0.5 mcg/day. If Rocaltrol therapy was previously administered at a dosage of 0.25 mcg/day, Rocaltrol therapy may be reinstituted at a dosage of 0.25 mcg every other day. If hypercalcemia is persistent at the reduced dosage, serum PTH should be measured. If serum PTH is normal, discontinue Rocaltrol therapy and monitor patient in 3 months' time.

Treatment of Hyperphosphatemia in Predialysis Patients

If serum phosphorus levels exceed 5.0 mg/dL to 5.5 mg/dL, a calcium-containing phosphate-binding agent (i.e., calcium carbonate or calcium acetate) should be taken with meals. Serum phosphorus levels should be determined as described earlier (see PRECAUTIONS: Laboratory Tests). Aluminum-containing gels should be used with caution as phosphate-binding agents because of the risk of slow aluminum accumulation.

Treatment of Accidental Overdosage of Rocaltrol

The treatment of acute accidental overdosage of Rocaltrol should consist of general supportive measures. If drug ingestion is discovered within a relatively short time, induction of emesis or gastric lavage may be of benefit in preventing further absorption. If the drug has passed through the stomach, the administration of mineral oil may promote its fecal elimination. Serial serum electrolyte determinations (especially calcium), rate of urinary calcium excretion, and assessment of electrocardiographic abnormalities due to hypercalcemia should be obtained. Such monitoring is critical in patients receiving digitalis. Discontinuation of supplemental calcium and a low-calcium diet are also indicated in accidental overdosage. Due to the relatively short duration of the pharmacological action of calcitriol, further measures are probably unnecessary. Should, however, persistent and markedly elevated serum calcium levels occur, there are a variety of therapeutic alternatives which may be considered, depending on the patient's underlying condition. These include the use of drugs such as phosphates and corticosteroids as well as measures to induce an appropriate forced diuresis. The use of peritoneal dialysis against a calcium-free dialysate has also been reported.

DOSAGE AND ADMINISTRATION

The optimal daily dose of Rocaltrol must be carefully determined for each patient. Rocaltrol can be administered orally either as a capsule (0.25 mcg or 0.50 mcg) or as an oral solution (1 mcg/mL). Rocaltrol therapy should always be started at the lowest possible dose and should not be increased without careful monitoring of serum calcium.

The effectiveness of Rocaltrol therapy is predicated on the assumption that each patient is receiving an adequate but not excessive daily intake of calcium. Patients are advised to have a dietary intake of calcium at a minimum of 600 mg daily. The U.S. RDA for calcium in adults is 800 mg to 1200 mg. To ensure that each patient receives an adequate daily intake of calcium, the physician should either prescribe a calcium supplement or instruct the patient in proper dietary measures.

Because of improved calcium absorption from the gastrointestinal tract, some patients on Rocaltrol may be maintained on a lower calcium intake. Patients who tend to develop hypercalcemia may require only low doses of calcium or no supplementation at all.

During the titration period of treatment with Rocaltrol, serum calcium levels should be checked at least twice weekly. When the optimal dosage of Rocaltrol has been determined, serum calcium levels should be checked every month (or as given below for individual indications). Samples for serum calcium estimation should be taken without a tourniquet.

Dialysis Patients

The recommended initial dose of Rocaltrol is 0.25 mcg/day. If a satisfactory response in the biochemical parameters and clinical manifestations of the disease state is not observed, dosage may be increased by 0.25 mcg/day at 4- to 8-week intervals. During this titration period, serum calcium levels should be obtained at least twice weekly, and if hypercalcemia is noted, the drug should be immediately discontinued until normocalcemia ensues (see PRECAUTIONS: General). Phosphorus, magnesium, and alkaline phosphatase should be determined periodically.

Patients with normal or only slightly reduced serum calcium levels may respond to Rocaltrol doses of 0.25 mcg every other day. Most patients undergoing hemodialysis respond to doses between 0.5 and 1 mcg/day.

Oral Rocaltrol may normalize plasma-ionized calcium in some uremic patients, yet fail to suppress parathyroid hyperfunction. In these individuals with autonomous parathyroid hyper-function, oral Rocaltrol may be useful to maintain normocalcemia, but has not been shown to be adequate treatment for hyperparathyroidism.

Hypoparathyroidism

The recommended initial dosage of Rocaltrol is 0.25 mcg/day given in the morning. If a satisfactory response in the biochemical parameters and clinical manifestations of the disease is not observed, the dose may be increased at 2- to 4-week intervals. During the dosage titration period, serum calcium levels should be obtained at least twice weekly and, if hypercalcemia is noted, Rocaltrol should be immediately discontinued until normocalcemia ensues (see PRECAUTIONS: General). Careful consideration should also be given to lowering the dietary calcium intake. Serum calcium, phosphorus, and 24-hour urinary calcium should be determined periodically.

Most adult patients and pediatric patients age 6 years and older have responded to dosages in the range of 0.5 mcg to 2 mcg daily. Pediatric patients in the 1- to 5-year age group with hypoparathyroidism have usually been given 0.25 mcg to 0.75 mcg daily. The number of treated patients with pseudohypoparathyroidism less than 6 years of age is too small to make dosage recommendations.

Malabsorption is occasionally noted in patients with hypoparathyroidism; hence, larger doses of Rocaltrol may be needed.

Predialysis Patients

The recommended initial dosage of Rocaltrol is 0.25 mcg/day in adults and pediatric patients 3 years of age and older. This dosage may be increased if necessary to 0.5 mcg/day.

For pediatric patients less than 3 years of age, the recommended initial dosage of Rocaltrol is 10 to 15 ng/kg/day.

HOW SUPPLIED

Capsules: 0.25 mcg calcitriol in soft gelatin, light orange, oval capsules, imprinted with R25; bottles of 30 (NDC 30698-143-23), and bottles of 100 (NDC 30698-143-01).

Capsules: 0.5 mcg calcitriol in soft gelatin, dark orange, oblong capsules, imprinted with R50; bottles of 100 (NDC 30698-144-01).

Oral Solution: a clear, colorless to pale yellow oral solution containing 1 mcg/mL of calcitriol; each amber glass bottle of 15 mL of oral solution supplied with 20 single-use, graduated oral dispensers (NDC 30698-911-15).

Rocaltrol Capsules and Oral Solution should be protected from light.

Store at 59° to 86°F (15° to 30°C) [See USP Controlled Room Temperature].

Dispense in a tight, light-resistant container as defined in USP.

REFERENCE

1. Jones CL, et al. Comparisons between oral and intraperitoneal 1,25-dihydroxyvitamin D3 therapy in children treated with peritoneal dialysis. Clin Nephrol. 1994; 42:44-49.

Manufactured for and Distributed by:

Validus Pharmaceuticals LLC
119 Cherry Hill Road, Suite 310
Parsippany, NJ 07054
info@validuspharma.com

www.validuspharma.com

1-866-982-5438 (1-866-9VALIDUS)

© 2018 Validus Pharmaceuticals LLC

60110-02 May 2018

PRINCIPAL DISPLAY PANEL

NDC 30698-143-01
ROCALTROL®
(calcitriol)
0.25 mcg
100 Capsules
Rx Only

PRINCIPAL DISPLAY PANEL

NDC 30698-143-23
ROCALTROL®
(calcitriol)
0.25 mcg
30 Capsules
Rx Only

PRINCIPAL DISPLAY PANEL

NDC 30698-144-01
ROCALTROL®
(calcitriol)
0.5 mcg
100 Capsules
Rx Only

PRINCIPAL DISPLAY PANEL

NDC 30698-911-15
ROCALTROL®
(calcitriol)
Oral Solution
1 mcg/mL
For Oral Use
Each mL contains 1 mcg calcitriol
15 mL
Rx Only